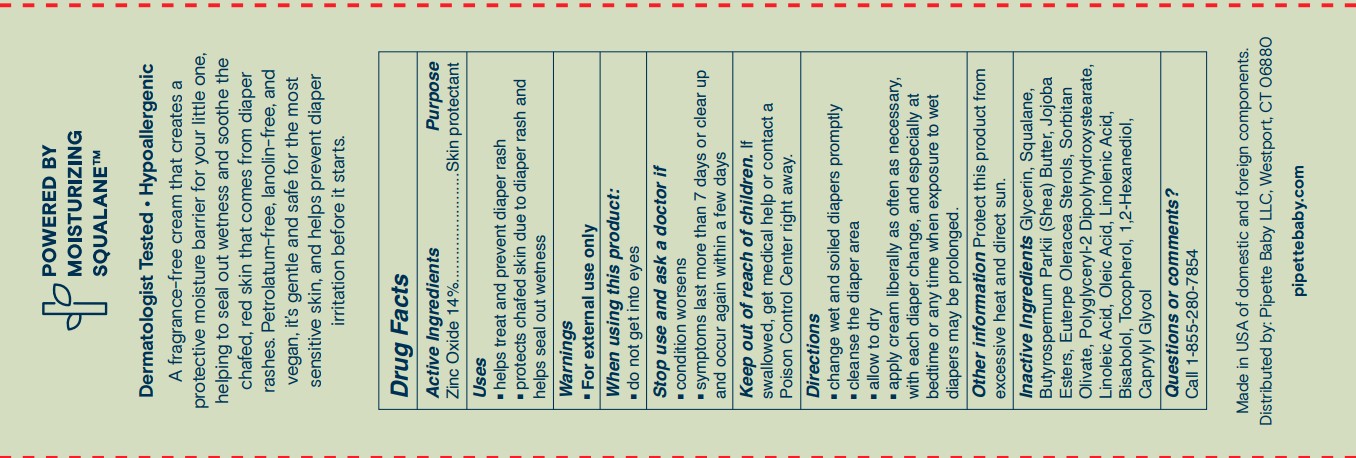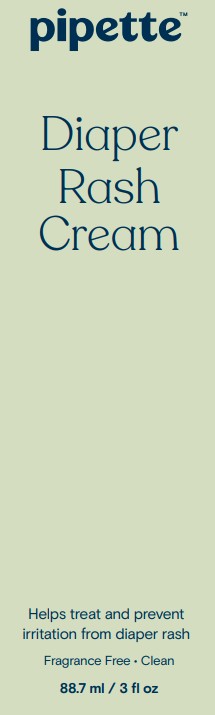 DRUG LABEL: Pipette Diaper Rash
NDC: 84723-007 | Form: CREAM
Manufacturer: Pipette LLC
Category: otc | Type: HUMAN OTC DRUG LABEL
Date: 20251114

ACTIVE INGREDIENTS: ZINC OXIDE 14 g/100 mL
INACTIVE INGREDIENTS: GLYCERIN; SQUALANE; BUTYROSPERMUM PARKII (SHEA) BUTTER UNSAPONIFIABLES; HYDROGENATED JOJOBA OIL/JOJOBA OIL, RANDOMIZED (IODINE VALUE 40-44); EUTERPE OLERACEA WHOLE; POLYGLYCERYL-2 DIPOLYHYDROXYSTEARATE; TOCOPHEROL; SORBITAN OLIVATE; 1,2-HEXANEDIOL; CAPRYLYL GLYCOL; LEVOMENOL; LINOLEIC ACID; OLEIC ACID; LINOLENIC ACID

Pipette Diaper Rash Cream

Active Ingredients

Zinc Oxide 14%

Purpose

Ski Protectant

Uses

- helps treat and prvent diaper rash
- protects chafed skin due to diaper rash and helps seal out wetness

Warnings

- For external use only

When using this product

- do not get into eyes

Stop use and aks a doctor if

- condition worsens
- symptoms last more than 7 days or clear up and occur again within a few days.

Keep out of reach of children

If swallowed, get medical help or contact a Poison Control Center right away.

Directions

- Change wet and soiled diapers promptly
- cleanse the diaper area
- allow to dry
- apply cream liberally as often as necessary, with each diaper change, and especially at betime or any time when exposure to wet diapers may be prolonged.

Other information

Protect this product from excessive heat and direct sunlight

Inactive Ingredients

Glycerin, Squalane, Butyrospermum Parkii (Shea) Butter, Jojoba Esters, Euterpe Oleracea Sterols,
Polyglyceryl-2 Dipolyhydroxystearate, Sorbitan Olivate, 1,2-Hexandiol, Caprylyl Glycol, Bisabolol, Linoleic Acid, Oleic
Acid, Linolenic Acid, Tocopherol.